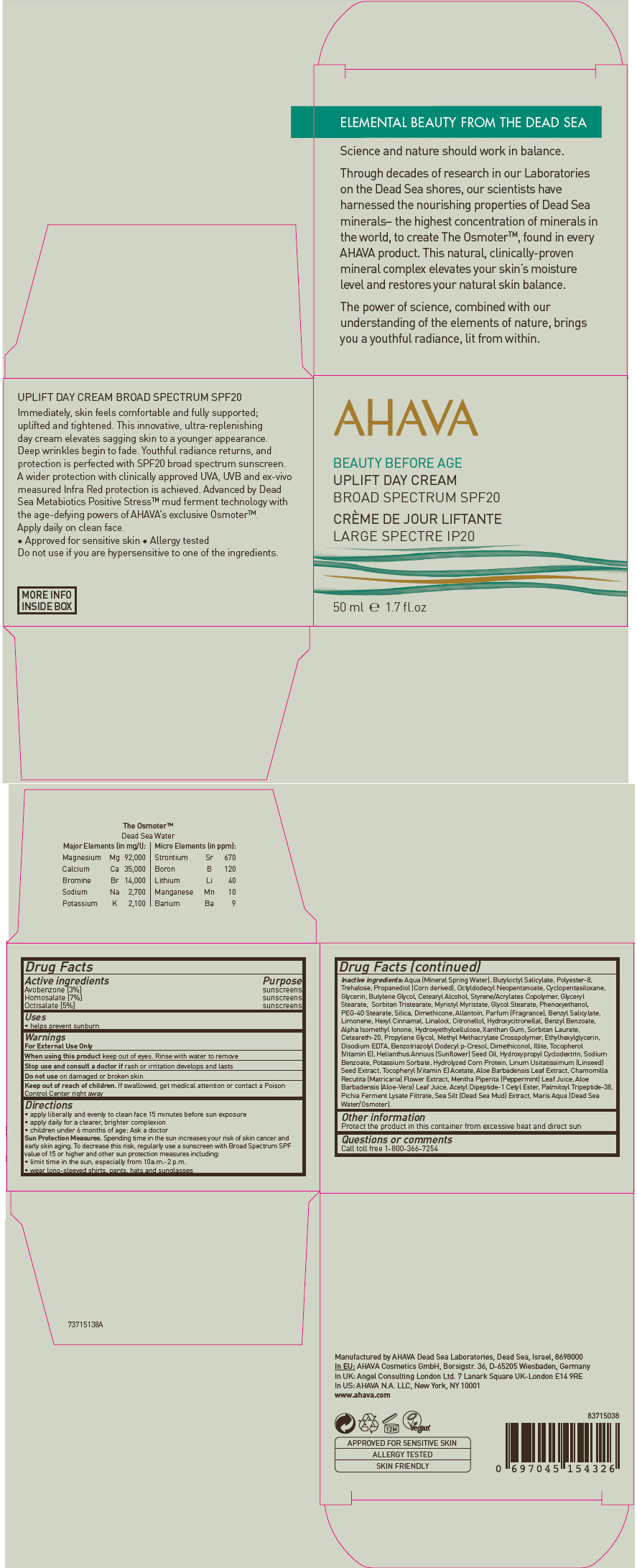 DRUG LABEL: BEAUTY BEFORE AGE 
NDC: 60289-283 | Form: CREAM
Manufacturer: AHAVA Dead Sea Laboratories Ltd
Category: otc | Type: HUMAN OTC DRUG LABEL
Date: 20231103

ACTIVE INGREDIENTS: Homosalate 3.5 g/50 mL; Octisalate 2.5 g/50 mL; Avobenzone 1.5 g/50 mL
INACTIVE INGREDIENTS: Water; Butyloctyl Salicylate; Butylene Glycol; Acetyl Tyrosylarginine Cetyl Ester; Sorbitan Monolaurate; CYCLOMETHICONE 5; Propanediol; Octyldodecyl Neopentanoate; Glyceryl Monostearate; PEG-100 Stearate; Trehalose; Myristyl Myristate; Glycerin; Palmitoyl Lysyldioxymethionyllysine; Flax Seed; Ethylhexylglycerin; Phenoxyethanol; Aloe Vera Leaf; Mentha Piperita Leaf; Dimethicone; Silicon Dioxide; Allantoin; Propylene Glycol; Chamomile; Xanthan Gum; .Alpha.-Tocopherol Acetate; Benzotriazolyl Dodecyl p-Cresol; .Alpha.-Tocopherol; Benzyl Salicylate; .Alpha.-Hexylcinnamaldehyde; Linalool, (+/-)-; .Beta.-Citronellol, (R)-; Hydroxycitronellal; POLYESTER-8 (1400 MW, CYANODIPHENYLPROPENOYL CAPPED); CETOSTEARYL ALCOHOL; BUTYL ACRYLATE/METHYL METHACRYLATE/METHACRYLIC ACID COPOLYMER (18000 MW); GLYCOL STEARATE; SORBITAN TRISTEARATE; PEG-40 STEARATE; POLYOXYL 20 CETOSTEARYL ETHER; HYDROXYETHYL CELLULOSE (4000 MPA.S AT 1%); HYDROXYPROPYL .ALPHA.-CYCLODEXTRIN; METHYL METHACRYLATE/GLYCOL DIMETHACRYLATE CROSSPOLYMER; LIMONENE, (-)-; Sodium Benzoate; Potassium Sorbate; SUNFLOWER OIL; LEDIKITE; Benzyl Benzoate; ISOMETHYL-.ALPHA.-IONONE

BEAUTY BEFORE AGE
AHAVA UPLIFT DAY CREAM broad spectrum SPF 20

Drug Facts

ACTIVE INGREDIENT

Active ingredients | Purpose
Avobenzone [3%] | sunscreens
Homosalate [7%] | sunscreens
Octisalate [5%] | sunscreens

Uses

- helps prevent sunburn

Warnings

For External Use Only

When using this product keep out of eyes. Rinse with water to remove

Stop use and consult a doctor if rash or irritation develops and lasts

Do not use on damaged or broken skin

Keep out of reach of children. If swallowed, get medical attention or contact a Poison Control Center right away

Directions

- apply liberally and evenly to clean face 15 minutes before sun exposure
- apply daily for a clearer, brighter complexion
- children under 6 months of age: Ask a doctor

Sun Protection Measures

Spending time in the sun increases your risk of skin cancer and early skin aging. To decrease this risk, regularly use a sunscreen with Broad Spectrum SPF value of 15 or higher and other sun protection measures including:

- limit time in the sun, especially from 10a.m.-2 p.m.
- wear long-sleeved shirts, pants, hats and sunglasses

Inactive ingredients

Aqua (Mineral Spring Water), Butyloctyl Salicylate, Polyester-8, Trehalose, Propanediol (Corn derived), Octyldodecyl Neopentanoate, Cyclopentasiloxane, Glycerin, Butylene Glycol, Cetearyl Alcohol, Styrene/Acrylates Copolymer, Glyceryl Stearate, Sorbitan Tristearate, Myristyl Myristate, Glycol Stearate, Phenoxyethanol, PEG-40 Stearate, Silica, Dimethicone, Allantoin, Parfum (Fragrance), Benzyl Salicylate, Limonene, Hexyl Cinnamal, Linalool, Citronellol, Hydroxycitronellal, Benzyl Benzoate, Alpha Isomethyl Ionone, Hydroxyethylcellulose, Xanthan Gum, Sorbitan Laurate, Ceteareth-20, Propylene Glycol, Methyl Methacrylate Crosspolymer, Ethylhexylglycerin, Disodium EDTA, Benzotriazolyl Dodecyl p-Cresol, Dimethiconol, Illite, Tocopherol (Vitamin E), Helianthus Annuus (Sunflower) Seed Oil, Hydroxypropyl Cyclodextrin, Sodium Benzoate, Potassium Sorbate, Hydrolyzed Corn Protein, Linum Usitatissimum (Linseed) Seed Extract, Tocopheryl (Vitamin E) Acetate, Aloe Barbadensis Leaf Extract, Chamomilla Recutita (Matricaria) Flower Extract, Mentha Piperita (Peppermint) Leaf Juice, Aloe Barbadensis (Aloe-Vera) Leaf Juice, Acetyl Dipeptide-1 Cetyl Ester, Palmitoyl Tripeptide-38, Pichia Ferment Lysate Filtrate, Sea Silt (Dead Sea Mud) Extract, Maris Aqua (Dead Sea Water/Osmoter).

Other information

Protect the product in this container from excessive heat and direct sun

Questions or comments

Call toll free 1-800-366-7254

Manufactured by AHAVA Dead Sea Laboratories, Dead Sea, Israel, 8698000
In US: AHAVA N.A. LLC, New York, NY 10001

PRINCIPAL DISPLAY PANEL - 50 ml Jar Carton

AHAVA

BEAUTY BEFORE AGE
UPLIFT DAY CREAM
BROAD SPECTRUM SPF20

50 ml ℮ 1.7 fl.oz